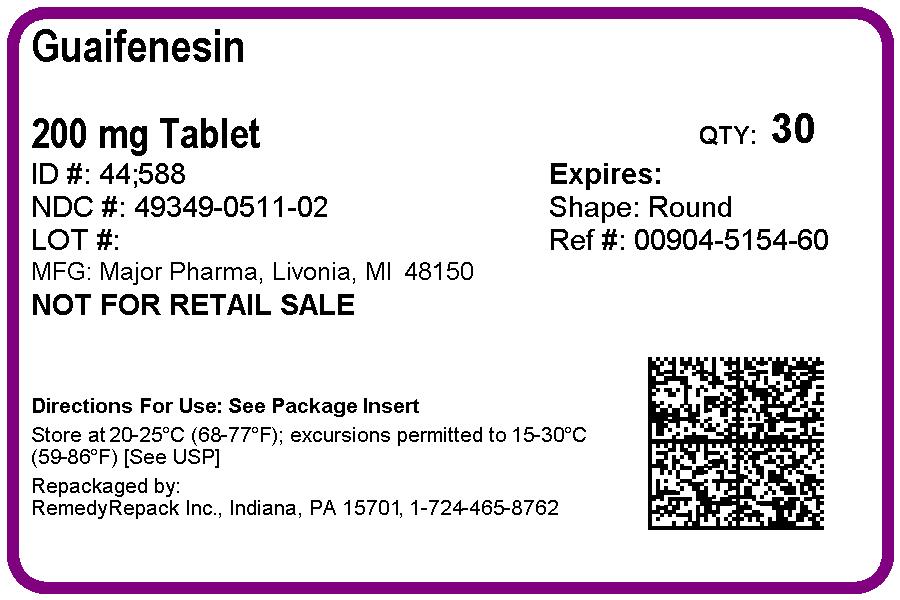 DRUG LABEL: Guaifenesin
NDC: 49349-511 | Form: TABLET
Manufacturer: REMEDYREPACK INC.
Category: otc | Type: HUMAN OTC DRUG LABEL
Date: 20170801

ACTIVE INGREDIENTS: GUAIFENESIN 200 mg/1 1
INACTIVE INGREDIENTS: MAGNESIUM STEARATE; MALTODEXTRIN; CELLULOSE, MICROCRYSTALLINE; POVIDONE; STEARIC ACID; FD&C RED NO. 40; SILICON DIOXIDE

Major 44-588

Active ingredient (in each immediate-release tablet)

Guaifenesin 200 mg

Purpose

Expectorant

Uses

helps loosen phlegm (mucus) and thin bronchial secretions to rid the bronchial passageways of bothersome mucus and make coughs more productive

Warnings

Ask a doctor before use if you have

- persistent or chronic cough such as occurs with smoking, asthma, chronic bronchitis, or emphysema
- cough accompanied by too much phlegm (mucus)

Stop use and ask a doctor if

cough lasts more than 7 days, comes back, or occurs with fever, rash, or persistent headache. These could be signs of a serious illness.

If pregnant or breast-feeding,

ask a health professional before use.

Keep out of reach of children.

In case of overdose, get medical help or contact a Poison Control Center right away.

Directions

- do not exceed 6 doses in 24 hours
- take with a full glass of water

adults and children 12 years of age and over | 1 to 2 tablets every 4 hours
children 6 to under 12 years of age | ½ to 1 tablet every 4 hours
children under 6 years of age | consult a physician

Other information

- store at 25ºC (77ºF); excursions permitted between 15º-30ºC (59º-86ºF)
- use by expiration date on package

Inactive ingredients

FD&C red #40 aluminum lake, magnesium stearate, maltodextrin, microcrystalline cellulose, povidone, silica gel, sodium starch glycolate, stearic acid

Questions or comments?

(800) 616-2471

PACKAGE LABEL

DRUG: Guaifenesin

GENERIC: Guaifenesin

DOSAGE: TABLET

ADMINSTRATION: ORAL

NDC: 49349-511-02

COLOR: pink

SHAPE: ROUND

SCORE: No score

SIZE: 10 mm

IMPRINT: 44;588

PACKAGING: 30 in 1 BLISTER PACK

ACTIVE INGREDIENT(S):

- GUAIFENESIN 200mg in 1

INACTIVE INGREDIENT(S):

- FD&C RED NO. 40
- MAGNESIUM STEARATE
- STEARIC ACID
- POVIDONE
- CELLULOSE, MICROCRYSTALLINE
- MALTODEXTRIN
- SILICON DIOXIDE